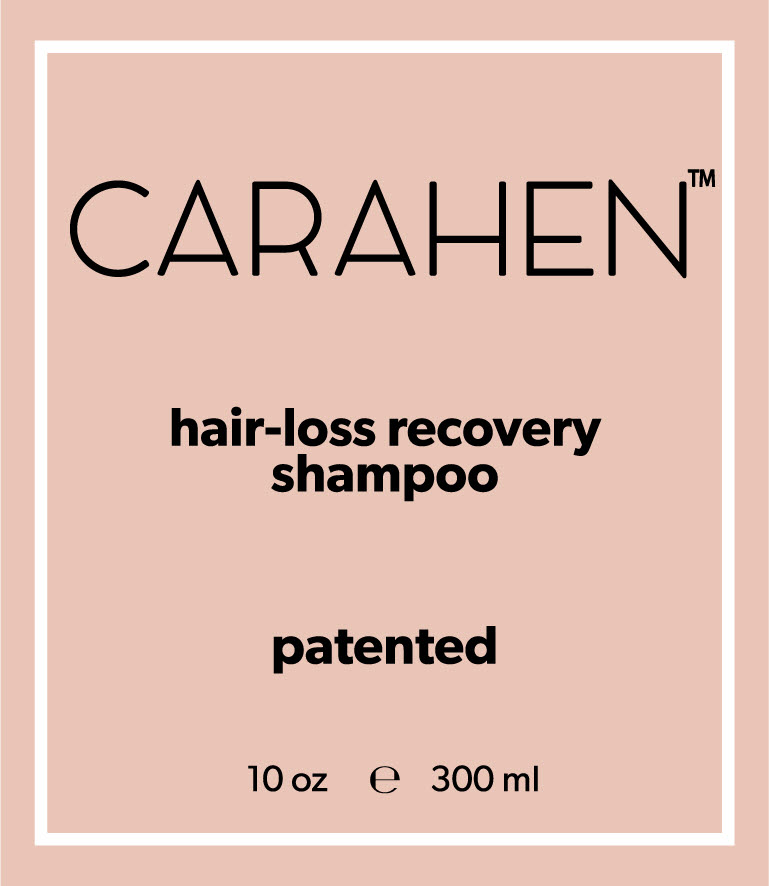 DRUG LABEL: Carahen scalp revitalizing serum mist
NDC: 71583-0001 | Form: LIQUID
Manufacturer: B.N.Trinity Co.,Ltd
Category: otc | Type: HUMAN OTC DRUG LABEL
Date: 20170720

ACTIVE INGREDIENTS: SALICYLIC ACID 0.2 g/100 mL
INACTIVE INGREDIENTS: BIOTIN

Drug Facts

ACTIVE INGREDIENT

Salicylic Acid

INACTIVE INGREDIENT

Biotin, etc

PURPOSE

Helps to scalp revitalizing

keep out of reach of the children

INDICATIONS AND USAGE

1. Spray on scalp with a distance of 20cm and massage gently.
2. Do not rinse and repeat several times as needed.

WARNINGS

1. Do not use in the following cases(Eczema and scalp wounds)
2.Side Effects
1)Due to the use of this druf if rash, irritation, itching and symptopms of hypersnesitivity occur dicontinue use and consult your phamacisr or doctor
3.General Precautions
1)If in contact with the eyes, wash out thoroughty with water If the symptoms are servere, seek medical advice immediately
2)This product is for exeternal use only. Do not use for internal use
4.Storage and handling precautions
1)If possible, avoid direct sunlight and store in cool and area of low humidity
2)In order to maintain the quality of the product and avoid misuse
3)Avoid placing the product near fire and store out in reach of children

DOSAGE AND ADMINISTRATION

for external use only